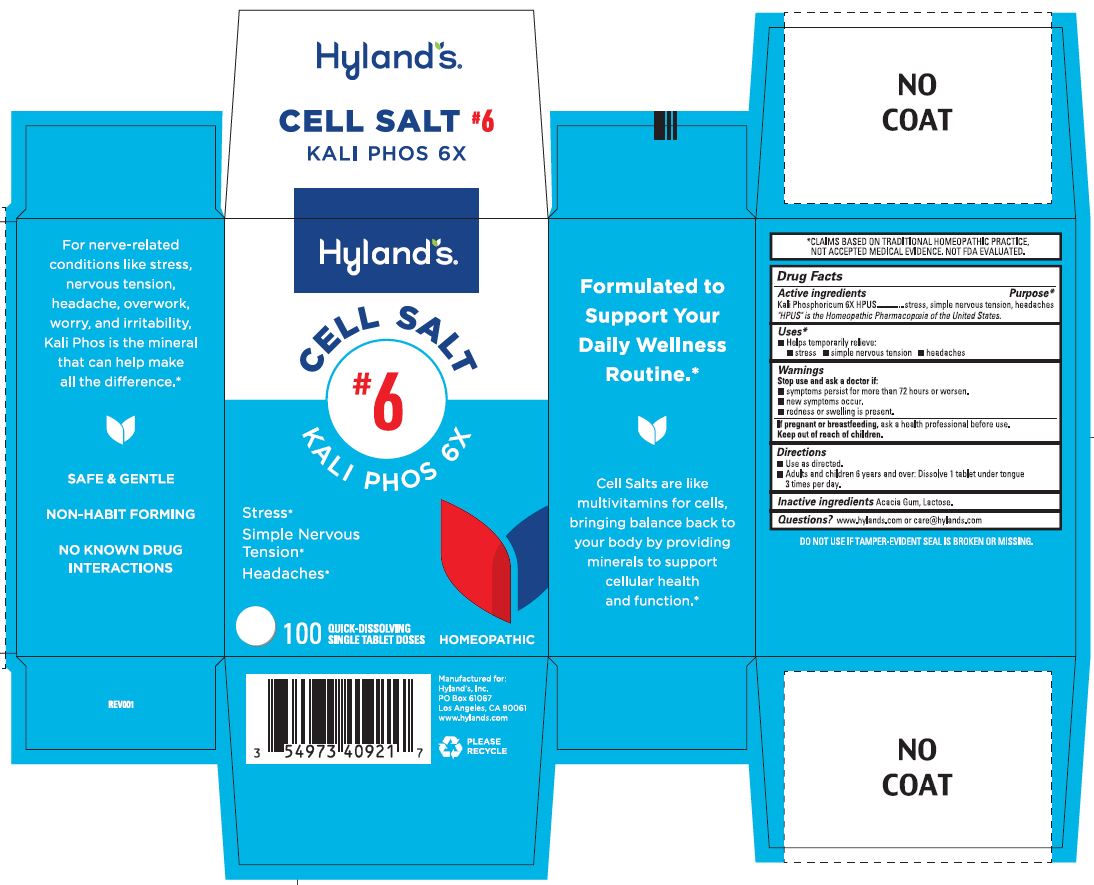 DRUG LABEL: Kali Phos 6X
NDC: 54973-4092 | Form: TABLET, SOLUBLE
Manufacturer: Hyland's Inc.
Category: homeopathic | Type: HUMAN OTC DRUG LABEL
Date: 20250430

ACTIVE INGREDIENTS: POTASSIUM PHOSPHATE, DIBASIC 6 [hp_X]/1 1
INACTIVE INGREDIENTS: ACACIA; LACTOSE MONOHYDRATE

Hyland's Cell Salt #6 Kali Phos 6X

PURPOSE

Stress

Simple Nervous Tension

Headaches

Drug Facts

Active ingredients | Purpose
Kali Phosphoricum 6X HPUS | stress, simple nervous tension, headaches

"HPUS" is the Homeopathic Pharmacopoeia of the United States.

Uses

■ Temporarily relieves:
■ stress ■ simple nervous tension ■ headaches

Warnings

Stop use and ask a doctor if

■ symptoms persist for more than 72 hours or worsen.
■ new symptoms occur.
■ redness or swelling is present.

If pregnant or breastfeeding

Ask a health professional before use.

Directions

■ Use as directed.
■ Adults and children 6 years and over: Dissolve 1 tablet under tongue 3 times per day.

Inactive ingredients

Acacia Gum, Lactose

Questions?

Acacia Gum, Lactose

PACKAGING LABEL - 100 TABLETS BOTTLE CARTON

Hyland's

CELL SALT

#6

KALI PHOS 6X

Stress*

Simple Nervous

Tension*

Headaches*

100

QUICK-DISSOLVING

SINGLE TABLET DOSES

HOMEOPATHIC